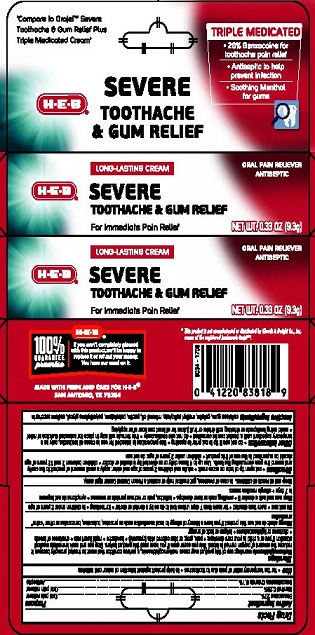 DRUG LABEL: HEB Severe Toothache and Gum Relief

NDC: 37808-313 | Form: CREAM
Manufacturer: HEB
Category: otc | Type: HUMAN OTC DRUG LABEL
Date: 20230111

ACTIVE INGREDIENTS: BENZALKONIUM CHLORIDE 0.1 g/100 g; BENZOCAINE 20 g/100 g; MENTHOL 0.25 g/100 g
INACTIVE INGREDIENTS: GELATIN; METHYL SALICYLATE; MINERAL OIL; PETROLATUM; PECTIN; SACCHARIN SODIUM; CARBOXYMETHYLCELLULOSE SODIUM, UNSPECIFIED FORM; POLYETHYLENE GLYCOL, UNSPECIFIED

HEB Severe Toothache & Gum Relief Triple Medicated Cream

Drug Facts

Active ingredients

Benzocaine 20%

Menthol 0.25%

Benzalkonium Chloride 0.1%

Purpose

Oral pain reliever

Oral pain reliever

Antiseptic

Use

- for the temporary relief of pain due to toothaches
- to help protect against infection of minor oral irritation

Warnings

Methemoglobenemia warning: use of this product may cause methemoglobinemia, a serious condition that must be treated promptly because it reduces the amount of oxygen carried in blood. This can occur even if you have used this product before. Stop use and seek immediate medical attention if you or a child in your care develops:

- pale, gray, or blue colored skin (cyanosis)
- headache
- rapid heart rate
- shortness of breath
- dizziness or lightheadedness
- fatigue or lack of energy

Allergy alert: do not use this product if you have a history of allergy to local anesthetics such as procaine, butacaine, benzocaine, or other "caine" anesthetics

Do not use

- more than directed
- for more than 7 days unless told to do so by a dentist or doctor
- for teething
- in children under 2 years of age

Stop use and ask a doctor if

- swelling, rash or fever develops
- irritation, pain or redness persists or worsens
- symptoms do not improve in 7 days
- allergic reaction occurs

Keep out of reach of children. In case of overdose, get medical help or contact a Poison Control Center right away.

Directions

- cut open tip of tube on score mark
- adults and children 2 years of age and older: apply a small amount of the product to the cavity and around the gum surrounding the teeth. Use up to 4 times daily or as directed by a dentist or doctor
- children between 2 and 12 years of age should be supervised in the use of this product
- children under 2 years of age: do not use

Other information

- do not use if tip is cut prior to opening
- this preparation is intended for use in cases of toothache, only as a temporary expedient until a dentist can be consulted
- do not use continuously
- this formula will stay in place for extended duration of relief
- avoid using toothpaste or drinking soft drinks or fruit juices for at least one hour after applying

INACTIVE INGREDIENT

Inactive ingredientscellulose gum, gelatin, methyl salicylate, mineral oil, pectin, polyethylene glycol, sodium saccharin

MADE WITH PRIDE AND CARE FOR H-E-B®

SAN ANTONIO, TX 78204

PACKAGE LABEL

H-E-B®

LONG LASTING CREAM

SEVERE TOOTHACHE & GUM RELIEF

ORAL PAIN RELIEVER

ANTISEPTIC

TRIPLE MEDICATED

- 20% Benzocaine for toothache pain relief
- Antiseptic to help prevent infection
- Soothing Menthol for gums

NET WT 0.33 OZ (9.3 g)